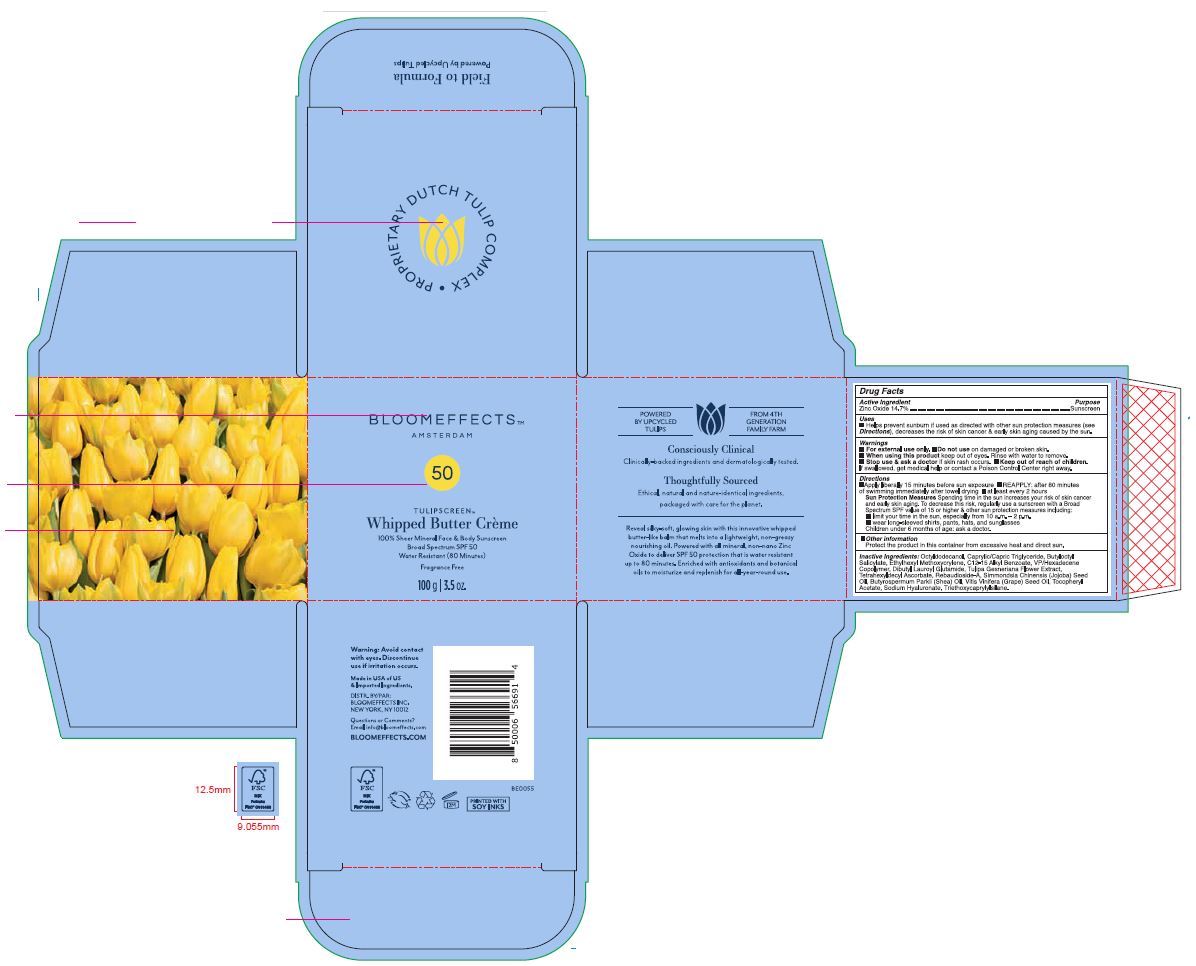 DRUG LABEL: Whipped Butter SPF 50
NDC: 82548-2421 | Form: CREAM
Manufacturer: Bloomeffects, Inc
Category: otc | Type: HUMAN OTC DRUG LABEL
Date: 20250723

ACTIVE INGREDIENTS: ZINC OXIDE 14.7 g/100 g
INACTIVE INGREDIENTS: BUTYROSPERMUM PARKII (SHEA) BUTTER; SIMMONDSIA CHINENSIS (JOJOBA) SEED OIL; .ALPHA.-TOCOPHEROL ACETATE; DIBUTYL LAUROYL GLUTAMIDE; REBAUDIOSIDE A; SODIUM HYALURONATE; C12-15 ALKYL BENZOATE; ETHYLHEXYL METHOXYCRYLENE; TULIPA GESNERIANA WHOLE; CAPRYLIC/CAPRIC TRIGLYCERIDE; TETRAHEXYLDECYL ASCORBATE; OCTYLDODECANOL; BUTYLOCTYL SALICYLATE; VP/HEXADECENE COPOLYMER; VITIS VINIFERA (GRAPE) SEED OIL; TRIETHOXYCAPRYLYLSILANE

Tulipscreen Whipped Butter Crème 100g / 3.5oz

ACTIVE INGREDIENT

Zinc Oxide 14.70%

PURPOSE

Sunscreen

INDICATIONS AND USAGE

Helps prevent sunburn if used as directed with other sun protection measures (see Directions), decreases the risk of skin cancer & early skin aging caused by the sun.

WARNINGS

For external use only.

Do not use on damaged or broken skin.

When using this product keep out of eyes. Rinse with water to remove.

Stop use & ask a doctor if skin rash occurs.

KEEP OUT OF REACH OF CHILDREN

Keep out of reach from children. If swallowed, get medical help or contact a Poison Control Center right away.

DOSAGE AND ADMINISTRATION

- Apply liberally 15 minutes before sun exposure
- Reapply: after 80 minutes of swimming immediately after towel drying | at least every 2 hours

Sun Protection Measures Spending time in the sun increases your risk of skin cancer and early skin aging. To decrease this risk, regularly use a sunscreen with a Broad Spectrum SPF value of 15 or higher & other sun protection measures including:

- limit your time in the sun, especially from 10 a.m - 2 p.m.
- wear long-sleeved shirts, pants, hats, and sunglasses

Children under 6 months of age: ask a doctor.

OTHER SAFETY INFORMATION

Protect the product in this container from excessive heat and direct sun.

INACTIVE INGREDIENT

Octyldodecanol

Caprylic/Capric Triglyceride

Butyloctyl Salicylate

Ethylhexyl Methoxycrylene

C12-15 Alkyl Benzoate

VP/Hexadecane Coplymer

Dibutyl Lauroyl Glutamide

Butrospermum Parkii (Shea) Oil

Rebaudioside-A

Simmondsia Chinensis (Jojoba) Seed Oil

Sodium Hyaluronate

Tetrahexyldecyl Ascorbate

Tocopheryl Acetate

Tulipa Gesneriana Flower Extract

Vitis Vinifera (Grape) Seed Oil

Triethoxycaprylylsilane